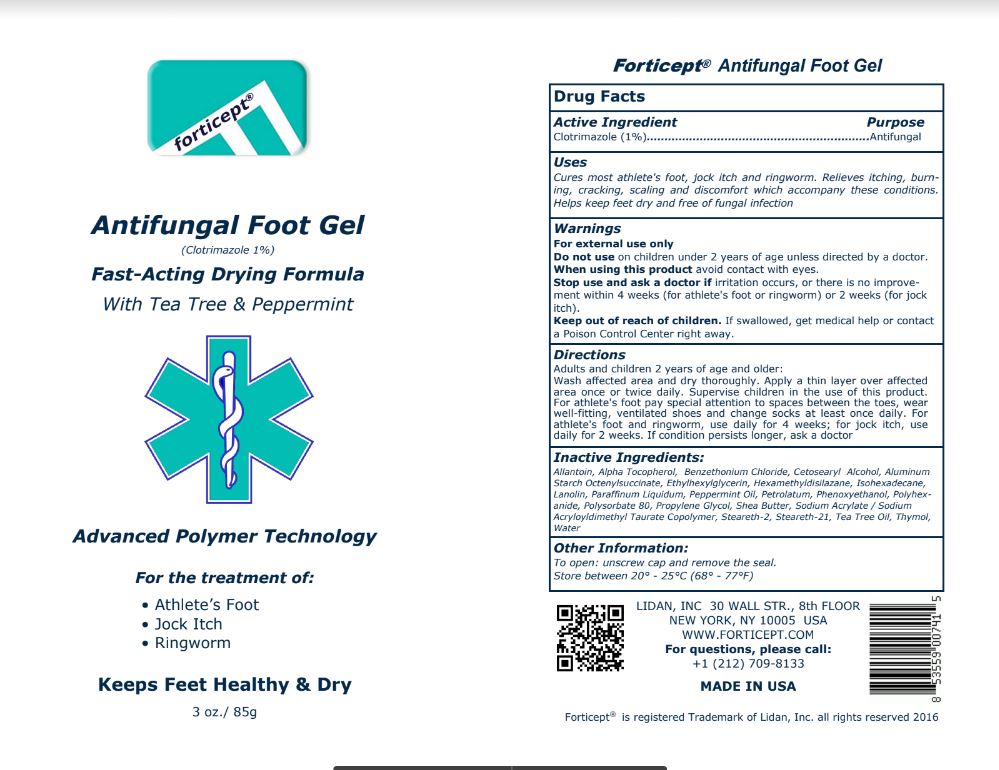 DRUG LABEL: Forticept Antifungal Foot Gel
NDC: 72127-0806 | Form: GEL
Manufacturer: Lidan, Inc.
Category: otc | Type: HUMAN OTC DRUG LABEL
Date: 20250325

ACTIVE INGREDIENTS: CLOTRIMAZOLE 0.01 kg/1 kg
INACTIVE INGREDIENTS: ALLANTOIN; .ALPHA.-TOCOPHEROL; ALUMINUM STARCH OCTENYLSUCCINATE; BENZETHONIUM CHLORIDE; CETOSTEARYL ALCOHOL; ETHYLHEXYLGLYCERIN; HEXAMETHYLDISILAZANE; ISOHEXADECANE; LANOLIN; MINERAL OIL; TEA TREE OIL; PEPPERMINT OIL; PETROLATUM; PHENOXYETHANOL; POLIHEXANIDE; POLYSORBATE 80; PROPYLENE GLYCOL; SHEA BUTTER; SODIUM ACRYLATE/SODIUM ACRYLOYLDIMETHYLTAURATE COPOLYMER (4000000 MW); Steareth-2; STEARETH-21; THYMOL; WATER

Forticept Antifungal Foot Gel

DRUG FACTS

Active Ingredient/Purpose

Clotrimazole - 1% (Antifungal)

Uses

• Cures most athlete's foot, jock itch and ringworm
• Relieves itching, burning, cracking, scaling and discomfort which accompany these conditions
• Helps keep feet dry and free of fungal infection

INDICATIONS AND USAGE

For the treatment of fungal infections caused by: Athlete's foot (tinea pedis), Jock itch (tinea cruris), and Ringworm (tinea corporis)

WARNINGS:

For external use only!

Keep out of reach of children. If swallowed, get medical help or contact a Poison Control Center right away

Do not use on children under 2 years of age unless directed by a doctor.

Stop use and ask a doctor if:
• irritation occurs
• there is no improvement within 4 weeks (for athlete's foot or ringworm) or 2 weeks (for jock itch).

When using this product avoid contact with eyes.

DIRECTIONS:

Adults and children 2 years of age and older:
• wash affected area and dry thoroughly
• apply a thin layer over affected area once or twice daily
• supervise children in the use of this product
• for athlete's foot, pay special attention to spaces between the toes, wear well-fitting, ventilated
• shoes and change socks at least once daily
• for athlete's foot and ringworm, use daily for 4 weeks; for jock itch, use daily for 2 weeks
• if condition persists longer, ask a doctor

Inactive Ingredients:

Allantoin, Alpha Tocopherol, Benzethonium Chloride, Cetosearyl Alcohol, Aluminum Starch Octenylsuccinate, Ethylhexylglycerin, Hexamethyldisilazane, Isohexadecane, Lanolin, Paraffinum Liquidum, Peppermint Oil, Petrolatum, Phenoxyethanol, Polyhexanide, Polysorbate 80, Propylene Glycol, Shea Butter, Sodium Acrylate / Sodium Acryloyldimethyl Taurate Copolymer, Steareth-2, Steareth-21, Tea Tree Oil, Thymol,
Water

Other Information:

• To open: unscrew cap and remove the seal.
• Store between 68° - 77°F (20° - 25°C)

For Questions:

Please call: +1 212 709-8133
Lidan, Inc.
30 Wall Street, 8th Floor
New York, NY 10005
www.forticept.com